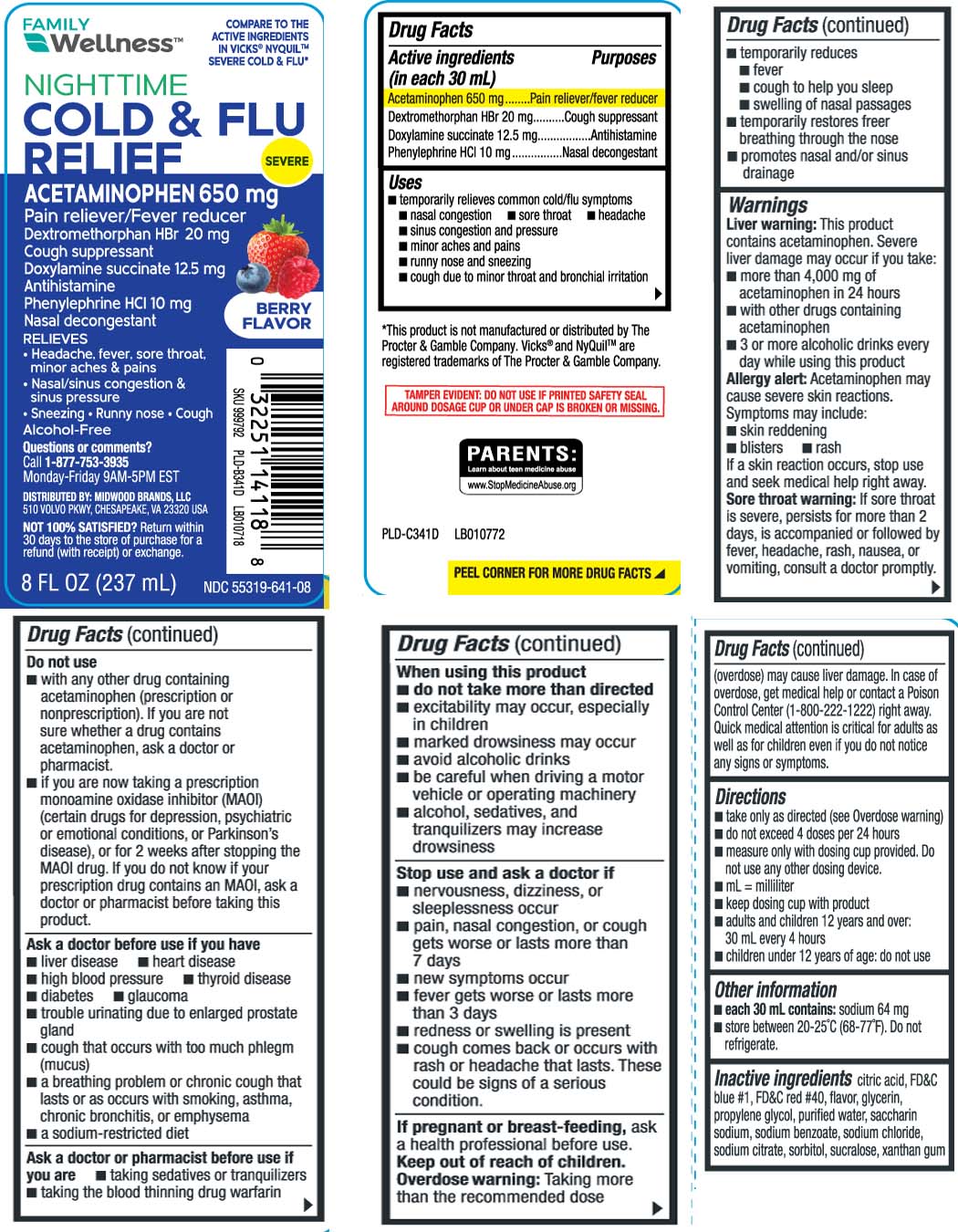 DRUG LABEL: Severe Nighttime Cold and Flu Relief
NDC: 55319-641 | Form: LIQUID
Manufacturer: Family Dollar (FAMILY WELLNESS)
Category: otc | Type: HUMAN OTC DRUG LABEL
Date: 20251124

ACTIVE INGREDIENTS: ACETAMINOPHEN 650 mg/30 mL; DEXTROMETHORPHAN HYDROBROMIDE 20 mg/30 mL; DOXYLAMINE SUCCINATE 12.5 mg/30 mL; PHENYLEPHRINE HYDROCHLORIDE 10 mg/30 mL
INACTIVE INGREDIENTS: PROPYLENE GLYCOL; WATER; ANHYDROUS CITRIC ACID; SACCHARIN SODIUM; FD&C BLUE NO. 1; FD&C RED NO. 40; TRISODIUM CITRATE DIHYDRATE; GLYCERIN; SODIUM BENZOATE; SODIUM CHLORIDE; SORBITOL; SUCRALOSE; XANTHAN GUM

Drug Facts

Active ingredients (in each 30 mL)

Acetaminophen 650 mg

Dextromethorphan HBr 20 mg

Doxylamine succinate 12.5 mg

Phenylephrine HCI 10 mg

Purposes

Pain reliever/fever reducer

Cough suppressant

Antihistamine

Nasal Decongestant

Uses

- temporarily relieves common cold/flu symptoms:
  - nasal congestion
  - sore throat
  - headache
  - sinus congestion and pressure
  - minor ache and pain
  - runny nose and sneezing
  - cough due to minor throat and bronchial irritation
- temporarily reduces
  - fever
  - cough to help you sleep
  - swelling of nasal passages
  - temporarily restores freer breathing through the nose
  - promotes nasal and/or sinus drainage

Warnings

Liver warning: This product contains acetaminophen. Severe liver damage may occur if you take

- more than 4,000 mg of acetaminophen in 24 hours
- with other drugs containing acetaminophen
- 3 or more alcoholic drinks everyday while using this product

Allergy alert: Acetaminophen may cause severe skin reactions. Symptoms may include:

- skin reddening
- blisters
- rash

If a skin reaction occurs, stop use and seek medical help right away.

Sore throat warning: If sore throat is severe, persists for more than 2 days, is accompanied or is followed by fever, headache, rash, nausea, or vomiting, consult a doctor promptly.

Do not use

- if you are now taking a prescription monoamine oxidase inhibitor (MAOI) (certain drugs for depression, psychiatric or emotional conditions, or Parkinson’s disease), or for 2 weeks after stopping the MAOI drug. If you do not know if your prescription drug contains an MAOI, ask a doctor or pharmacist before taking this product.
- with any other drug containing acetaminophen (prescription or non-prescription). If you are not sure whether a drug contains acetaminophen, ask a doctor or pharmacist

Ask a doctor before use if you have

- liver disease
- heart disease
- high blood pressure
- thyroid disease
- diabetes
- glaucoma
- trouble urinating due to an enlarges prostate gland
- cough that occurs with too much phlegm (mucus)
- a breathing problem or chronic cough that lasts or as occurs with smoking, asthma, chronic bronchitis, or emphysema
- a sodium-restricted diet

Ask a doctor or pharmacist before use if you are taking

- taking sedatives or tranquilizers
- taking the blood thinning drug warfarin

When using this product

- do not use more than directed
- excitability may occur, especially in children
- marked drowsiness may occur
- avoid alcoholic drinks
- be careful when driving a motor vehicle or operating machinery
- alcohol, sedatives and tranquilizers may increase drowsiness

Stop use and ask a doctor if

- nervousness, dizziness, or sleeplessness occur
- pain, nasal congestion, or cough gets worse or lasts more than 7 days
- new symptoms occur
- fever gets worse or last more than 3 days
- redness or swelling is present
- cough comes back, or occurs with rash or headache that lasts.

These could be a signs of a serious conditions.

If pregnant or breast-feeding,

ask a health professional before use.

Keep out of reach of children.

Overdose warning: Taking more than the recommended dose (overdose) may cause liver damage. In case of overdose, get medical help or contact a Poison Control Center (1-800-222-1222) right away. Quick medical attention is critical even if you do not notice any signs or symptoms.

Directions

- take only as directed - see Overdose warning
- do not exceed 4 doses per 24 hours
- measure only with dosing cup provided. Do not use any other dosing device.
- mL = milliliter
- keep dosing cup with product
- adults and children 12 years and over: 30 mL every 4 hours
- children under 12 years of age: do not use
- When using Daytime or Nighttime products, carefully read each label to ensure correct dosing.

Other information

- each 30 mL contains; sodium 64 mg
- store between 20-25ºC (68-77ºF). Do not refrigerate

Inactive ingredients

anhydrous citric acid. FD&C blue1, FD&C red 40, Flavor, glycerin, propylene glycol, purified water, saccharin sodium, sodium benzoate, sodium chloride, sorbitol, sucralose, trisodium citrate dihydrate, xanthan gum

Questions or comments?

Call 1-877-753-3935 Monday-Friday 9AM-5PM EST

Principal Display Panel

COMPARE TO THE ACTIVE INGREDIENTS IN VICKS® NYQUIL™ SEVERE COLD & FLU*

NIGHTTIME

COLD & FLU RELIEF

ACETAMINOPHEN 650 mg

Pain Reliever/Fever Reducer

Dextromethorphan HBr 20 mg

Cough suppressant

Doxylamine succinate 12.5 mg

Antihistamine

Phenylephrine HCI 10 mg

Nasal decongestant

Relieves

- Headache, fever, sore throat, minor aches & pains
- Nasal/sinus congestion & sinus pressure
- Sneezing
- Runny nose
- Cough

Alcohol free

FL OZ (mL)

BERRY FLAVOR

*This product is not manufactured or distributed by The Procter & Gamble Company. Vicks® and NyQuil™ are registered trademarks of The Procter & Gamble Company.

TAMPER EVIDENT: DO NOT USE IF PRINTED SAFETY SEAL AROUND DOSAGE CUP OR UNDER CAP IS BROKEN OR MISSING.

DISTRIBUTED BY: MIDWOOD BRANDS, LLC

510 VOLVO PKWY, CHESAPEAKE, VA 23320

Product Label

FAMILY WELLNESS Nighttime Cold & Flu Relief